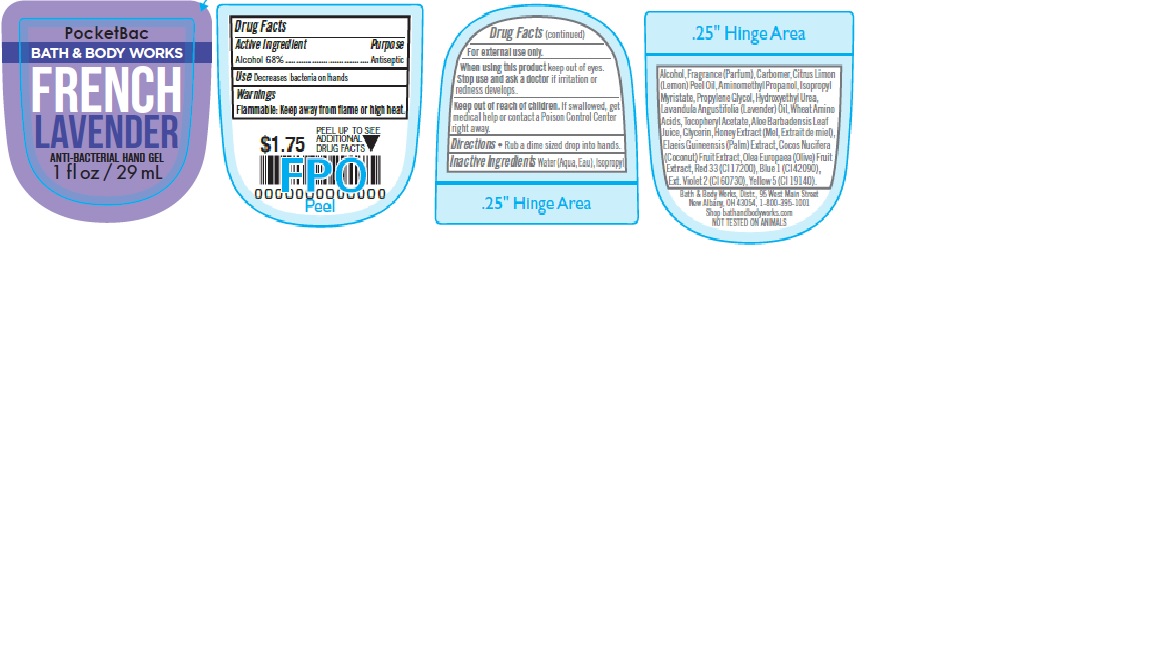 DRUG LABEL: Anti-Bacterial Hand
NDC: 62670-5442 | Form: GEL
Manufacturer: Bath & Body Works, Inc.
Category: otc | Type: HUMAN OTC DRUG LABEL
Date: 20180629

ACTIVE INGREDIENTS: ALCOHOL 68 mL/100 mL
INACTIVE INGREDIENTS: WATER

ACTIVE INGREDIENT

Alcohol 68%

PURPOSE

Antiseptic

USE

Decreases bacteria on hands.

WARNINGS

For external use only.

WHEN USING THIS PRODUCT

keep out of eyes.

STOP USE AND ASK A DOCTOR

if irritation or redness develops.

FLAMMABLE

Keep away from flame or high heat.

KEEP OUT OF REACH OF CHILDREN

If swallowed, get medical help or contact a Poison Control Center right away.

DIRECTIONS

- Rub a dime sized drop into hands.

INACTIVE INGREDIENTS

Water (Aqua, Eau), Isopropyl Alcohol, Fragrance (Parfum), Carbomer, Citrus Limon (Lemon) Peel Oil, Aminomethyl Propanol, Isopropyl Myristate, Propylene Glycol, Hydroxyethyl Urea, Lavandula Angustifolia (Lavender) Oil, Wheat Amino Acids, Tocopheryl Acetate, Aloe Barbadensis Leaf Juice, Glycerin, Honey Extract (Mel, Extrait de miel), Elaeis Guineensis (Palm) Extract, Cocos Nucifera (Coconut) Fruit Extract, Olea Europaea (Olive) Fruit Extract, Red 33 (CI 17200), Blue 1 (CI 42090), Ext. Violet 2 (CI 60730), Yellow 5 (CI 19140).

COMPANY INFORMATION

Bath & Body Works, Distr., 95 West Main Street

New Albany, OH, 43054, 1-800-395-1001

Shop 24/7 at www.bathandbodyworks.com